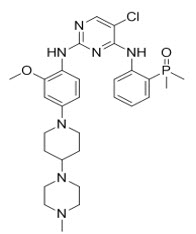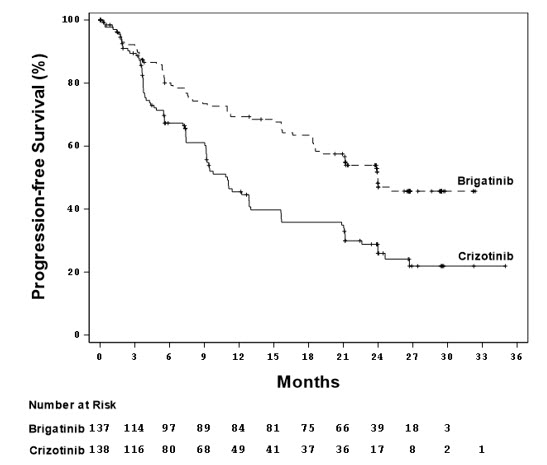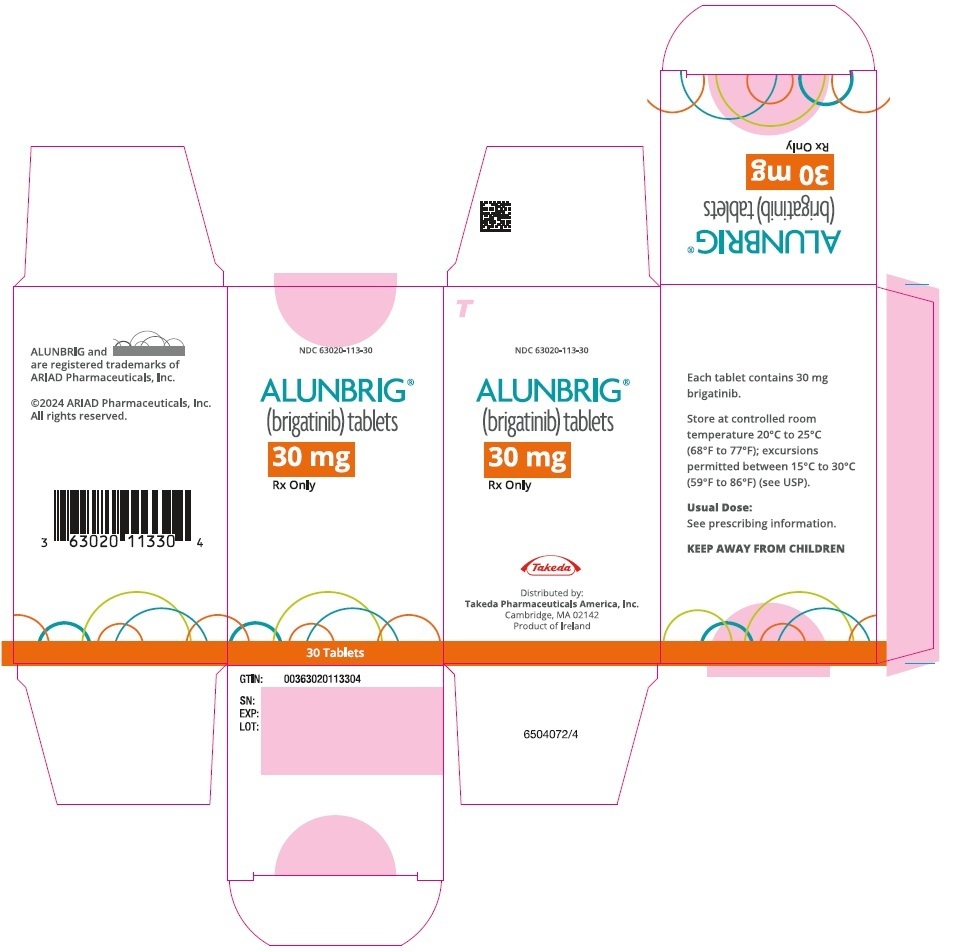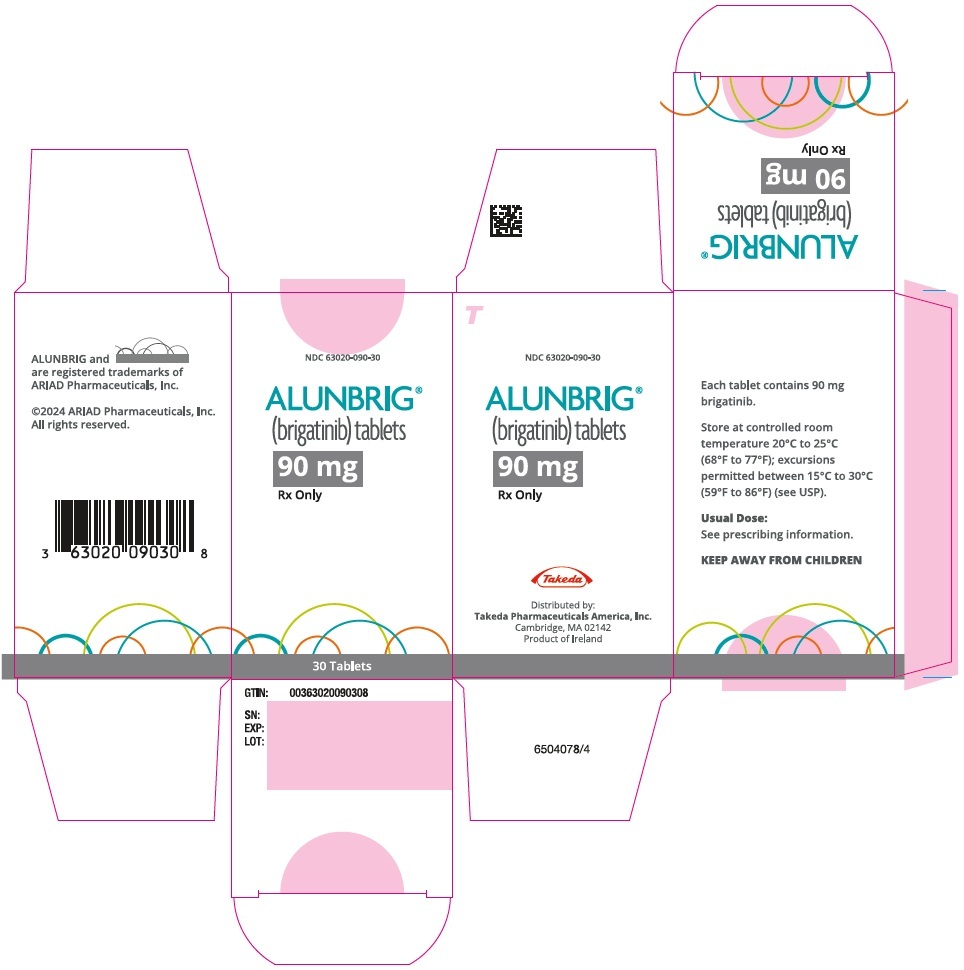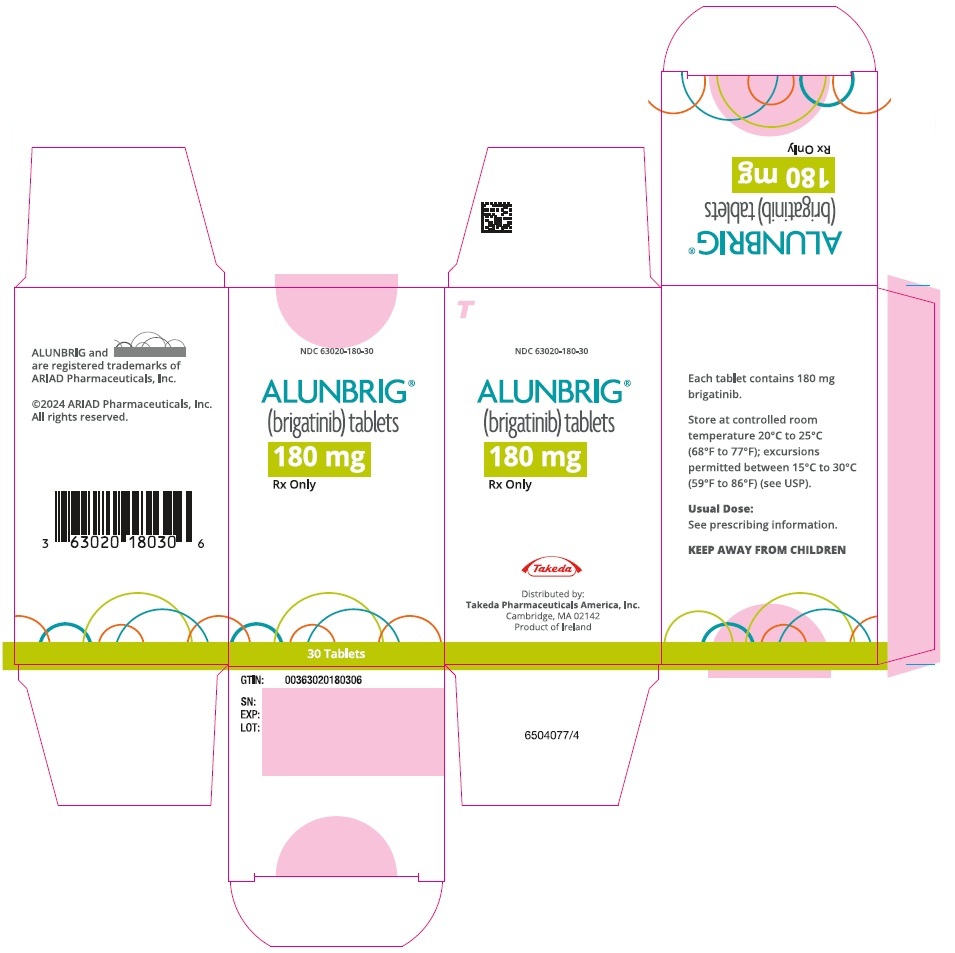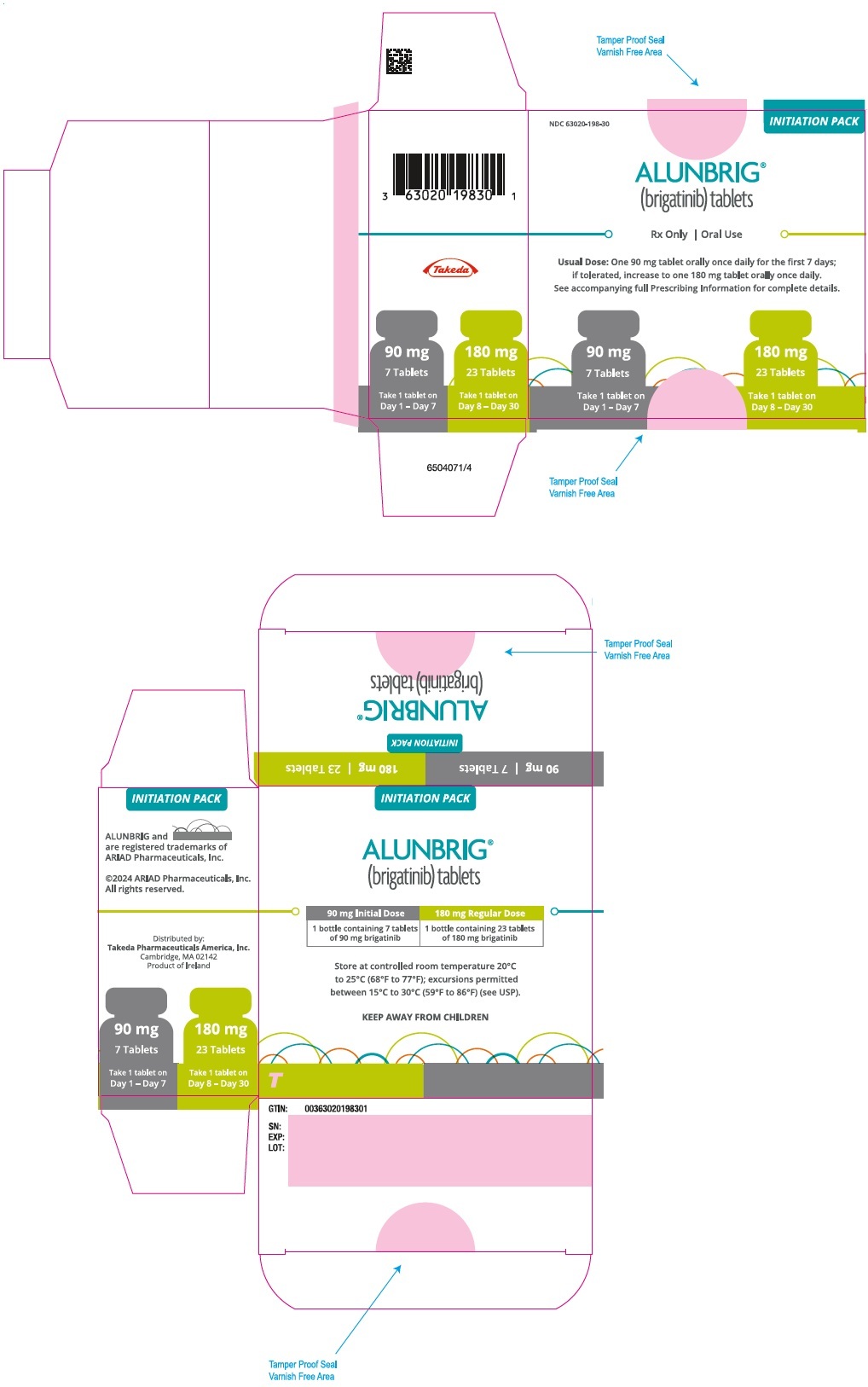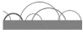 DRUG LABEL: Alunbrig
NDC: 63020-113 | Form: TABLET, FILM COATED
Manufacturer: Takeda Pharmaceuticals America, Inc.
Category: prescription | Type: HUMAN PRESCRIPTION DRUG LABEL
Date: 20260112

ACTIVE INGREDIENTS: brigatinib 30 mg/1 1
INACTIVE INGREDIENTS: Lactose monohydrate; Microcrystalline cellulose; SODIUM STARCH GLYCOLATE TYPE A POTATO; SILICON DIOXIDE; Magnesium stearate

HIGHLIGHTS OF PRESCRIBING INFORMATION

These highlights do not include all the information needed to use ALUNBRIG safely and effectively. See full prescribing information for ALUNBRIG.
ALUNBRIG® (brigatinib) tablets, for oral use
Initial U.S. Approval: 2017

1 INDICATIONS AND USAGE

ALUNBRIG is a kinase inhibitor indicated for the treatment of adult patients with anaplastic lymphoma kinase (ALK)-positive metastatic non-small cell lung cancer (NSCLC) as detected by an FDA-approved test. (1, 2.1)

2 DOSAGE AND ADMINISTRATION

90 mg orally once daily for the first 7 days; then increase to 180 mg orally once daily. May be taken with or without food. (2.2)

3 DOSAGE FORMS AND STRENGTHS

Tablets: 180 mg, 90 mg, or 30 mg. (3)

4 CONTRAINDICATIONS

None. (4)

5 WARNINGS AND PRECAUTIONS

- Interstitial Lung Disease (ILD)/Pneumonitis: Monitor for new or worsening respiratory symptoms, particularly during the first week of treatment. Withhold ALUNBRIG for new or worsening respiratory symptoms and promptly evaluate for ILD/pneumonitis. Upon recovery, either dose reduce or permanently discontinue ALUNBRIG. (2.3, 5.1)
- Hypertension: Monitor blood pressure after 2 weeks and then at least monthly during treatment. For severe hypertension, withhold ALUNBRIG, then dose reduce or permanently discontinue. (2.3, 5.2)
- Bradycardia: Monitor heart rate and blood pressure regularly during treatment. If symptomatic, withhold ALUNBRIG, then dose reduce or permanently discontinue. (2.3, 5.3)
- Visual Disturbance: Advise patients to report visual symptoms. Withhold ALUNBRIG and obtain ophthalmologic evaluation, then dose reduce or permanently discontinue ALUNBRIG. (2.3, 5.4)
- Creatine Phosphokinase (CPK) Elevation: Monitor CPK levels regularly during treatment. Based on the severity and with muscle pain or weakness, withhold ALUNBRIG, then resume or reduce dose. (2.3, 5.5)
- Pancreatic Enzymes Elevation: Monitor lipase and amylase levels regularly during treatment. Based on the severity, withhold ALUNBRIG, then resume or reduce dose. (2.3, 5.6)
- Hepatotoxicity: Monitor alanine aminotransferase (ALT), aspartate aminotransferase (AST) and total bilirubin levels regularly during treatment. Based on severity, withhold dose, then resume at lower level. (2.3, 5.7)
- Hyperglycemia: Assess fasting serum glucose prior to starting ALUNBRIG and regularly during treatment. If not adequately controlled with optimal medical management, withhold ALUNBRIG, then consider dose reduction or permanently discontinue, based on severity. (2.3, 5.8)
- Photosensitivity: Advise patients to limit sun exposure. Based on severity withhold ALUNBRIG, then resume at the same dose, reduce the dose, or permanently discontinue. (2.3, 5.9)
- Embryo-Fetal Toxicity: Can cause fetal harm. Advise females of reproductive potential of the potential risk to a fetus and to use effective contraception. (5.10, 8.1, 8.3)

6 ADVERSE REACTIONS

The most common adverse reactions (≥25%) with ALUNBRIG were diarrhea, fatigue, nausea, rash, cough, myalgia, headache, hypertension, vomiting, and dyspnea. (6.1)

To report SUSPECTED ADVERSE REACTIONS, contact Takeda Pharmaceuticals at 1-844-217-6468 or FDA at 1-800-FDA-1088 or www.fda.gov/medwatch.

7 DRUG INTERACTIONS

- CYP3A Inhibitors: Avoid coadministration of ALUNBRIG with strong or moderate CYP3A inhibitors. If coadministration of a strong or moderate CYP3A inhibitor is unavoidable, reduce the dose of ALUNBRIG. (2.4, 7.1)
- CYP3A Inducers: Avoid coadministration of ALUNBRIG with strong or moderate CYP3A inducers. If coadministration of a moderate CYP3A inducer is unavoidable, increase the dose of ALUNBRIG. (2.5, 7.1)

8 USE IN SPECIFIC POPULATIONS

- Hepatic Impairment: Reduce the dose of ALUNBRIG for patients with severe hepatic impairment. (2.6, 8.6)
- Renal Impairment: Reduce the dose of ALUNBRIG for patients with severe renal impairment. (2.7, 8.7)
- Lactation: Advise not to breastfeed. (8.2)

FULL PRESCRIBING INFORMATION

1 INDICATIONS AND USAGE

ALUNBRIG is indicated for the treatment of adult patients with anaplastic lymphoma kinase (ALK)-positive metastatic non-small cell lung cancer (NSCLC) as detected by an FDA-approved test [see Dosage and Administration (2.1)].

2 DOSAGE AND ADMINISTRATION

2.1 Patient Selection

Select patients for the treatment of metastatic NSCLC with ALUNBRIG based on the presence of ALK positivity in tumor specimens [see Clinical Studies (14)].

Information on FDA-approved tests for the detection of ALK rearrangements in NSCLC is available at http://www.fda.gov/CompanionDiagnostics.

2.2 Recommended Dosage

The recommended dosage for ALUNBRIG is:

- 90 mg orally once daily for the first 7 days; then increase the dose to 180 mg orally once daily.

Administer ALUNBRIG until disease progression or unacceptable toxicity.

If ALUNBRIG is interrupted for 14 days or longer for reasons other than adverse reactions, resume treatment at 90 mg once daily for 7 days before increasing to the previously tolerated dose.

ALUNBRIG may be taken with or without food. Instruct patients to swallow tablets whole. Do not crush or chew tablets.

If a dose of ALUNBRIG is missed or vomiting occurs after taking a dose, do not administer an additional dose and take the next dose of ALUNBRIG at the scheduled time.

2.3 Dosage Modifications for Adverse Reactions

ALUNBRIG dosage reductions for adverse reactions are summarized in Table 1.

Table 1: Recommended ALUNBRIG Dosage Reductions
 | Dosage Reduction
Dosage | First | Second | Third
90 mg once daily | 60 mg once daily | permanently discontinue | N/A [Not applicable]
180 mg once daily | 120 mg once daily | 90 mg once daily | 60 mg once daily

Once reduced for adverse reactions, do not subsequently increase the dosage of ALUNBRIG. Permanently discontinue ALUNBRIG if patients are unable to tolerate the 60 mg once daily dose.

Recommendations for dosage modifications of ALUNBRIG for the management of adverse reactions are provided in Table 2.

Table 2: Recommended ALUNBRIG Dosage Modifications for Adverse Reactions
Adverse Reaction | Severity [Graded per National Cancer Institute Common Terminology Criteria for Adverse Events. Version 4.0 (NCI CTCAE v4).] | Dosage Modifications
Interstitial Lung Disease (ILD) /Pneumonitis [see Warnings and Precautions (5.1)] | Grade 1 | - If new pulmonary symptoms occur during the first 7 days of treatment, withhold ALUNBRIG until recovery to baseline, then resume at same dose and do not escalate to 180 mg if ILD/pneumonitis is suspected. - If new pulmonary symptoms occur after the first 7 days of treatment, withhold ALUNBRIG until recovery to baseline, then resume at same dose. - If ILD/pneumonitis recurs, permanently discontinue ALUNBRIG.
Interstitial Lung Disease (ILD) /Pneumonitis [see Warnings and Precautions (5.1)] | Grade 2 | - If new pulmonary symptoms occur during the first 7 days of treatment, withhold ALUNBRIG until recovery to baseline. Resume at next lower dose (Table 1) and do not dose escalate if ILD/pneumonitis is suspected. - If new pulmonary symptoms occur after the first 7 days of treatment, withhold ALUNBRIG until recovery to baseline. If ILD/pneumonitis is suspected, resume at next lower dose (Table 1); otherwise, resume at same dose. - If ILD/pneumonitis recurs, permanently discontinue ALUNBRIG.
Interstitial Lung Disease (ILD) /Pneumonitis [see Warnings and Precautions (5.1)] | Grade 3 or 4 | Permanently discontinue ALUNBRIG for ILD/pneumonitis.
Hypertension [see Warnings and Precautions (5.2)] | Grade 3 hypertension (SBP greater than or equal to 160 mmHg or DBP greater than or equal to 100 mmHg, medical intervention indicated, more than one antihypertensive drug, or more intensive therapy than previously used indicated) | - Withhold ALUNBRIG until hypertension has recovered to Grade 1 or less (SBP less than 140 mmHg and DBP less than 90 mmHg), then resume ALUNBRIG at the same dose. - Recurrence: withhold ALUNBRIG until recovery to Grade 1 or less, and resume at next lower dose (Table 1) or permanently discontinue treatment.
Hypertension [see Warnings and Precautions (5.2)] | Grade 4 hypertension (life-threatening consequences, urgent intervention indicated) | - Withhold ALUNBRIG until recovery to Grade 1 or less, and resume at next lower dose (Table 1) or permanently discontinue treatment. - Recurrence: permanently discontinue ALUNBRIG for recurrence of Grade 4 hypertension.
Bradycardia (HR less than 60 bpm) [see Warnings and Precautions (5.3)] | Symptomatic bradycardia | - Withhold ALUNBRIG until recovery to asymptomatic bradycardia or to a resting heart rate of 60 bpm or above. - If a concomitant medication known to cause bradycardia is identified and discontinued or dose-adjusted, resume ALUNBRIG at same dose upon recovery to asymptomatic bradycardia or to resting heart rate of 60 bpm or above. - If no concomitant medication known to cause bradycardia is identified, or if contributing concomitant medications are not discontinued or dose-adjusted, resume ALUNBRIG at next lower dose (Table 1) upon recovery to asymptomatic bradycardia or to resting heart rate of 60 bpm or above.
Bradycardia (HR less than 60 bpm) [see Warnings and Precautions (5.3)] | Bradycardia with life-threatening consequences, urgent intervention indicated | - Permanently discontinue ALUNBRIG if no contributing concomitant medication is identified. - If contributing concomitant medication is identified and discontinued or dose-adjusted, resume ALUNBRIG at next lower dose (Table 1) upon recovery to asymptomatic bradycardia or to a resting heart rate of 60 bpm or above, with frequent monitoring as clinically indicated. - Recurrence: permanently discontinue ALUNBRIG.
Visual Disturbance [see Warnings and Precautions (5.4)] | Grade 2 or 3 visual disturbance | Withhold ALUNBRIG until recovery to Grade 1 or baseline, then resume at the next lower dose (Table 1).
Visual Disturbance [see Warnings and Precautions (5.4)] | Grade 4 visual disturbance | Permanently discontinue ALUNBRIG.
Creatine Phosphokinase (CPK) Elevation [see Warnings and Precautions (5.5)] | Grade 3 or 4 CPK elevation (greater than 5× ULN) with Grade 2 or higher muscle pain or weakness | - Withhold ALUNBRIG until recovery to Grade 1 or less (less than or equal to 2.5× ULN) CPK elevation or to baseline, then resume ALUNBRIG at same dose. - Recurrence: Withhold ALUNBRIG until recovery to Grade 1 or less (less than or equal to 2.5× ULN) CPK elevation or to baseline, then resume ALUNBRIG at the next lower dose (Table 1).
Lipase/Amylase Elevation [see Warnings and Precautions (5.6)] | Grade 3 lipase or amylase elevation (greater than 2× ULN) | - Withhold ALUNBRIG until recovery to Grade 1 or less (less than or equal to 1.5× ULN) or to baseline, then resume ALUNBRIG at same dose. - Recurrence: Withhold ALUNBRIG until recovery to Grade 1 or less (less than or equal to 1.5× ULN) or to baseline, then resume ALUNBRIG at next lower dose (Table 1).
Lipase/Amylase Elevation [see Warnings and Precautions (5.6)] | Grade 4 lipase or amylase elevation (greater than 5× ULN) | Withhold ALUNBRIG until recovery to Grade 1 or less (less than or equal to 1.5× ULN) or to baseline, then resume ALUNBRIG at next lower dose (Table 1).
Hepatotoxicity (Elevation of alanine aminotransferase (ALT) or aspartate aminotransferase (AST)) [see Warnings and Precautions (5.7)] | Grade 3 or 4 elevation (greater than 5 × ULN) of either ALT or AST with bilirubin less than or equal to 2 × ULN | Withhold ALUNBRIG until recovery to Grade 1 or less (less than or equal to 3× ULN) or to baseline, then resume ALUNBRIG at next lower dose (Table 1).
Hepatotoxicity (Elevation of alanine aminotransferase (ALT) or aspartate aminotransferase (AST)) [see Warnings and Precautions (5.7)] | Grade 2 to 4 elevation (greater than 3 × ULN) of ALT or AST with concurrent total bilirubin elevation greater than 2 × ULN in the absence of cholestasis or hemolysis | Permanently discontinue ALUNBRIG.
Hyperglycemia [see Warnings and Precautions (5.8)] | Grade 3 (greater than 250 mg/dL or 13.9 mmol/L) or 4 | If adequate hyperglycemic control cannot be achieved with optimal medical management, withhold ALUNBRIG until adequate hyperglycemic control is achieved and resume at the next lower dose (Table 1) or permanently discontinue ALUNBRIG.
Other | Grade 3 | - Withhold ALUNBRIG until recovery to baseline, then resume at same dose. - Recurrence: withhold ALUNBRIG until recovery to baseline, then resume at next lower dose or discontinue ALUNBRIG (Table 1).
Other | Grade 4 | - Withhold ALUNBRIG until recovery to baseline and resume at next lower dose (Table 1). - Recurrence: Permanently discontinue ALUNBRIG.
bpm = beats per minute; DBP = diastolic blood pressure; HR = heart rate; SBP = systolic blood pressure; ULN = upper limit of normal

2.4 Dosage Modifications for Strong or Moderate CYP3A Inhibitors

Avoid coadministration of strong or moderate CYP3A inhibitors during treatment with ALUNBRIG [see Drug Interactions (7.1), Clinical Pharmacology (12.3)]. If coadministration of a strong CYP3A inhibitor cannot be avoided, reduce the ALUNBRIG once daily dose by approximately 50% (i.e., from 180 mg to 90 mg, or from 90 mg to 60 mg). If coadministration of a moderate CYP3A inhibitor cannot be avoided, reduce the ALUNBRIG once daily dose by approximately 40% (i.e., from 180 mg to 120 mg, 120 mg to 90 mg, or from 90 mg to 60 mg). After discontinuation of a strong or moderate CYP3A inhibitor, resume the ALUNBRIG dose that was tolerated prior to initiating the CYP3A inhibitor.

2.5 Dosage Modifications for Moderate CYP3A Inducers

Avoid coadministration of moderate CYP3A inducers during treatment with ALUNBRIG [see Drug Interactions (7.1), Clinical Pharmacology (12.3)]. If coadministration of a moderate CYP3A inducer cannot be avoided, increase the ALUNBRIG once daily dose in 30 mg increments after 7 days of treatment with the current ALUNBRIG dose as tolerated, up to a maximum of twice the ALUNBRIG dose that was tolerated prior to initiating the moderate CYP3A inducer.

After discontinuation of a moderate CYP3A inducer, resume the ALUNBRIG dose that was tolerated prior to initiating the moderate CYP3A inducer.

2.6 Dosage Modifications for Patients with Severe Hepatic Impairment

Reduce the ALUNBRIG once daily dose by approximately 40% (i.e., from 180 mg to 120 mg, 120 mg to 90 mg, or from 90 mg to 60 mg) for patients with severe hepatic impairment (Child-Pugh C) [see Use in Specific Populations (8.6), Clinical Pharmacology (12.3)].

2.7 Dosage Modifications for Patients with Severe Renal Impairment

Reduce the ALUNBRIG once daily dose by approximately 50% (i.e., from 180 mg to 90 mg, or from 90 mg to 60 mg) for patients with severe renal impairment [creatinine clearance (CLcr) 15 to 29 mL/min by Cockcroft-Gault] [see Use in Specific Populations (8.7), Clinical Pharmacology (12.3)].

3 DOSAGE FORMS AND STRENGTHS

- 180 mg: oval, white to off-white film-coated tablets with "U13" debossed on one side and plain on the other side
- 90 mg: oval, white to off-white film-coated tablets with "U7" debossed on one side and plain on the other side
- 30 mg: round, white to off-white film-coated tablets with "U3" debossed on one side and plain on the other side

4 CONTRAINDICATIONS

None.

5 WARNINGS AND PRECAUTIONS

5.1 Interstitial Lung Disease (ILD)/Pneumonitis

Severe, life-threatening, and fatal pulmonary adverse reactions consistent with interstitial lung disease (ILD)/pneumonitis have occurred with ALUNBRIG.

In Trial ALTA 1L, ILD/pneumonitis occurred in 5.1% of patients receiving ALUNBRIG. ILD/pneumonitis occurred within 8 days of initiation of ALUNBRIG in 2.9% of patients, with Grade 3 to 4 reactions occurring in 2.2% of patients.

In Trial ALTA, ILD/pneumonitis occurred in 3.7% of patients in the 90 mg group (90 mg once daily) and 9.1% of patients in the 90→180 mg group (180 mg once daily with 7-day lead-in at 90 mg once daily). Adverse reactions consistent with possible ILD/pneumonitis occurred within 9 days of initiation of ALUNBRIG (median onset was 2 days) in 6.4% of patients, with Grade 3 to 4 reactions occurring in 2.7%.

Monitor for new or worsening respiratory symptoms (e.g., dyspnea, cough, etc.), particularly during the first week of initiating ALUNBRIG. Withhold ALUNBRIG in any patient with new or worsening respiratory symptoms, and promptly evaluate for ILD/pneumonitis or other causes of respiratory symptoms (e.g., pulmonary embolism, tumor progression, and infectious pneumonia). For Grade 1 or 2 ILD/pneumonitis, either resume ALUNBRIG with dose reduction according to Table 1 after recovery to baseline or permanently discontinue ALUNBRIG. Permanently discontinue ALUNBRIG for Grade 3 or 4 ILD/pneumonitis or recurrence of Grade 1 or 2 ILD/pneumonitis [see Dosage and Administration (2.3), Adverse Reactions (6.1)].

5.2 Hypertension

In ALTA 1L, hypertension was reported in 32% of patients receiving ALUNBRIG; Grade 3 hypertension occurred in 13% of patients.

In ALTA, hypertension was reported in 11% of patients in the 90 mg group who received ALUNBRIG and 21% of patients in the 90→180 mg group. Grade 3 hypertension occurred in 5.9% of patients overall.

Control blood pressure prior to treatment with ALUNBRIG. Monitor blood pressure after 2 weeks and at least monthly thereafter during treatment with ALUNBRIG. Withhold ALUNBRIG for Grade 3 hypertension despite optimal antihypertensive therapy. Upon resolution or improvement to Grade 1, resume ALUNBRIG at the same dose. Consider permanent discontinuation of treatment with ALUNBRIG for Grade 4 hypertension or recurrence of Grade 3 hypertension [see Dosage and Administration (2.3), Adverse Reactions (6.1)].

Use caution when administering ALUNBRIG in combination with antihypertensive agents that cause bradycardia [see Warnings and Precautions (5.3)].

5.3 Bradycardia

In ALTA 1L, heart rates less than 50 beats per minute (bpm) occurred in 8.1% of patients receiving ALUNBRIG. Grade 3 bradycardia occurred in 1 patient (0.7%).

In ALTA, heart rates less than 50 beats per minute (bpm) occurred in 5.7% of patients in the 90 mg group and 7.6% of patients in the 90→180 mg group. Grade 2 bradycardia occurred in 1 (0.9%) patient in the 90 mg group.

Monitor heart rate and blood pressure during treatment with ALUNBRIG. Monitor patients more frequently if concomitant use of drug known to cause bradycardia cannot be avoided [see Warnings and Precautions (5.2)].

For symptomatic bradycardia, withhold ALUNBRIG and review concomitant medications for those known to cause bradycardia. If a concomitant medication known to cause bradycardia is identified and discontinued or dose adjusted, resume ALUNBRIG at the same dose following resolution of symptomatic bradycardia; otherwise, reduce the dose of ALUNBRIG following resolution of symptomatic bradycardia. Discontinue ALUNBRIG for life-threatening bradycardia if no contributing concomitant medication is identified [see Dosage and Administration (2.3)].

5.4 Visual Disturbance

In ALTA 1L, Grade 1 or 2 adverse reactions leading to visual disturbance including blurred vision, photophobia, photopsia, and reduced visual acuity were reported in 7.4% of patients receiving ALUNBRIG.

In ALTA, adverse reactions leading to visual disturbance including blurred vision, diplopia, and reduced visual acuity, were reported in 7.3% of patients receiving ALUNBRIG in the 90 mg group and 10% of patients in the 90→180 mg group. Grade 3 macular edema and cataract occurred in 1 patient each in the 90→180 mg group.

Advise patients to report any visual symptoms. Withhold ALUNBRIG and obtain an ophthalmologic evaluation in patients with new or worsening visual symptoms of Grade 2 or greater severity. Upon recovery of Grade 2 or Grade 3 visual disturbances to Grade 1 severity or baseline, resume ALUNBRIG at a reduced dose. Permanently discontinue treatment with ALUNBRIG for Grade 4 visual disturbances [see Dosage and Administration (2.3), Adverse Reactions (6.1)].

5.5 Creatine Phosphokinase (CPK) Elevation

In ALTA 1L, creatine phosphokinase (CPK) elevation occurred in 81% of patients who received ALUNBRIG. The incidence of Grade 3 or 4 CPK elevation was 24%. Dose reduction for CPK elevation occurred in 15% of patients.

In ALTA, CPK elevation occurred in 27% of patients receiving ALUNBRIG in the 90 mg group and 48% of patients in the 90 mg→180 mg group. The incidence of Grade 3 to 4 CPK elevation was 2.8% in the 90 mg group and 12% in the 90→180 mg group.

Dose reduction for CPK elevation occurred in 1.8% of patients in the 90 mg group and 4.5% in the 90→180 mg group.

Advise patients to report any unexplained muscle pain, tenderness, or weakness. Monitor CPK levels during ALUNBRIG treatment. Withhold ALUNBRIG for Grade 3 or 4 CPK elevation with Grade 2 or higher muscle pain or weakness. Upon resolution or recovery to Grade 1 CPK elevation or baseline, resume ALUNBRIG at the same dose or at a reduced dose as described in Table 2 [see Dosage and Administration (2.3), Adverse Reactions (6.1)].

5.6 Pancreatic Enzymes Elevation

In ALTA 1L, amylase elevation occurred in 52% of patients and Grade 3 or 4 amylase elevation occurred in 6.8% of patients. Lipase elevations occurred in 59% of patients and Grade 3 or 4 lipase elevation occurred in 17% of patients.

In ALTA, amylase elevation occurred in 27% of patients in the 90 mg group and 39% of patients in the 90→180 mg group. Lipase elevations occurred in 21% of patients in the 90 mg group and 45% of patients in the 90→180 mg group. Grade 3 or 4 amylase elevation occurred in 3.7% of patients in the 90 mg group and 2.7% of patients in the 90→180 mg group. Grade 3 or 4 lipase elevation occurred in 4.6% of patients in the 90 mg group and 5.5% of patients in the 90→180 mg group.

Monitor lipase and amylase during treatment with ALUNBRIG. Withhold ALUNBRIG for Grade 3 or 4 pancreatic enzyme elevation. Upon resolution or recovery to Grade 1 or baseline, resume ALUNBRIG at the same dose or at a reduced dose as described in Table 2 [see Dosage and Administration (2.3), Adverse Reactions (6.1)].

5.7 Hepatotoxicity

In ALTA 1L, aspartate aminotransferase (AST) elevations occurred in 72% of patients and Grade 3 or 4 AST elevations occurred in 4.5% of patients. Alanine aminotransferase (ALT) elevations occurred in 52% of patients and Grade 3 or 4 ALT elevations occurred in 5.2% of patients. One patient (0.7%) had a serious adverse reaction of hepatocellular injury.

In ALTA, AST elevations occurred in 38% of patients in the 90 mg group and 65% of patients in the 90→180 mg group. ALT elevations occurred in 34% of patients in the 90 mg group and 40% of patients in the 90→180 mg group. Grade 3 or 4 AST elevations occurred in 0.9% of patients in the 90 mg group and did not occur in any patients in the 90→180 mg group. Grade 3 or 4 ALT elevations did not occur in any patients in the 90 mg group and in 2.7% of patients in the 90→180 mg group.

Monitor AST, ALT and total bilirubin during treatment with ALUNBRIG, especially during first 3 months. Withhold ALUNBRIG for Grade 3 or 4 hepatic enzyme elevation with bilirubin less than or equal to 2 × ULN. Upon resolution or recovery to Grade 1 or less (less than or equal to 3 × ULN) or to baseline, resume ALUNBRIG at a next lower dose as described in Table 2. Permanently discontinue ALUNBRIG for Grade 2 to 4 hepatic enzyme elevation with concurrent total bilirubin elevation greater than 2 times the ULN in the absence of cholestasis or hemolysis [see Dosage and Administration (2.3), Adverse Reactions (6.1)].

5.8 Hyperglycemia

In ALTA 1L, 56% of patients who received ALUNBRIG experienced new or worsening hyperglycemia. Grade 3 hyperglycemia, based on laboratory assessment of serum fasting glucose levels, occurred in 7.5% of patients.

In ALTA, 43% of patients who received ALUNBRIG experienced new or worsening hyperglycemia. Grade 3 hyperglycemia, based on laboratory assessment of serum fasting glucose levels, occurred in 3.7% of patients. Two of 20 (10%) patients with diabetes or glucose intolerance at baseline required initiation of insulin while receiving ALUNBRIG.

Assess fasting serum glucose prior to initiation of ALUNBRIG and monitor periodically thereafter. Initiate or optimize antihyperglycemic medications as needed. If adequate hyperglycemic control cannot be achieved with optimal medical management, withhold ALUNBRIG until adequate hyperglycemic control is achieved and consider reducing the dose of ALUNBRIG as described in Table 1 or permanently discontinuing ALUNBRIG [see Dosage and Administration (2.3), Adverse Reactions (6.1)].

5.9 Photosensitivity

In ALTA 1L, photosensitivity occurred in 3.7% of patients who received ALUNBRIG, with 0.7% Grade 3 to 4.

In ALTA, 0.9% of patients who received ALUNBRIG in the 90 mg group experienced photosensitivity and 0.9% of patients in the 90 mg→180 mg group. Grade 3 to 4 photosensitivity was not reported in patients in the 90 mg group or in the 90→180 mg group.

Advise patients to limit sun exposure while taking brigatinib, and for at least 5 days after discontinuation of treatment. Advise patients, when outdoors to wear a hat and protective clothing, and use a broad-spectrum Ultraviolet A (UVA)/ Ultraviolet B (UVB) sunscreen and lip balm (SPF ≥30) to help protect against sunburn. Based on the severity withhold ALUNBRIG, then resume at the same dose, or reduce the dose, or permanently discontinue as described in Table 2 [see Dosage and Administration (2.3), Adverse Reactions (6.1)].

5.10 Embryo-Fetal Toxicity

Based on its mechanism of action and findings in animals, ALUNBRIG can cause fetal harm when administered to pregnant women. There are no clinical data on the use of ALUNBRIG in pregnant women. Administration of brigatinib to pregnant rats during the period of organogenesis resulted in dose-related skeletal anomalies at doses as low as 12.5 mg/kg/day (approximately 0.7 times the human exposure by AUC at 180 mg once daily), as well as increased post-implantation loss, malformations, and decreased fetal body weight at doses of 25 mg/kg/day (approximately 1.26 times the human exposure at 180 mg once daily) or higher.

Advise women of the potential risk to a fetus. Advise females of reproductive potential to use effective contraception during treatment with ALUNBRIG and for at least 4 months following the final dose. Advise males with female partners of reproductive potential to use effective contraception during treatment and for at least 3 months after the last dose of ALUNBRIG [see Use in Specific Populations (8.1, 8.3), Clinical Pharmacology (12.1)].

6 ADVERSE REACTIONS

The following adverse reactions are discussed in greater detail in other sections of the prescribing information:

- Interstitial Lung Disease (ILD)/Pneumonitis [see Warnings and Precautions (5.1)]
- Hypertension [see Warnings and Precautions (5.2)]
- Bradycardia [see Warnings and Precautions (5.3)]
- Visual Disturbance [see Warnings and Precautions (5.4)]
- Creatine Phosphokinase (CPK) Elevation [see Warnings and Precautions (5.5)]
- Pancreatic Enzymes Elevation [see Warnings and Precautions (5.6)]
- Hepatotoxicity [see Warnings and Precautions (5.7)]
- Hyperglycemia [see Warnings and Precautions (5.8)]
- Photosensitivity [see Warnings and Precautions (5.9)]

6.1 Clinical Trials Experience

Because clinical trials are conducted under widely varying conditions, adverse reaction rates observed in the clinical trials of a drug cannot be directly compared to rates in the clinical trials of another drug and may not reflect the rates observed in practice.

Advanced ALK-positive NSCLC Without Prior ALK-targeted Therapy

In ALTA 1L, the safety of ALUNBRIG was evaluated in 136 patients with advanced ALK-positive NSCLC who had not previously received an ALK-targeted therapy [see Clinical Studies (14)]. The median duration of treatment with ALUNBRIG when administered as 90 mg orally once daily for the first 7 days; then increased to 180 mg orally once daily, was 24.3 months. A total of 106 (78%) patients were exposed to ALUNBRIG for greater than or equal to 6 months including 92 (68%) patients exposed for greater than or equal to 1 year. The median relative dose intensity was 97% for ALUNBRIG.

The study population (N = 275) characteristics were: median age 59 years (range: 27 to 89), age less than 65 years (68%), female (55%), White (59%), Asian (39%), Stage IV disease (93%), NSCLC adenocarcinoma histology (96%), never smoker (58%), ECOG Performance Status (PS) 0 or 1 (95%), and CNS metastases at baseline (30%) [see Clinical Studies (14)].

Serious adverse reactions occurred in 33% of patients receiving ALUNBRIG. The most common serious adverse reactions were pneumonia (4.4%), ILD/pneumonitis (3.7%), pyrexia (2.9%), dyspnea (2.2%), pulmonary embolism (2.2%), and asthenia (2.2%). Fatal adverse reactions occurred in 2.9% of patients and included pneumonia (1.5%), cerebrovascular accident (0.7%), and multiple organ dysfunction syndrome (0.7%).

In ALTA 1L, 13% of patients receiving ALUNBRIG permanently discontinued ALUNBRIG for adverse reactions. The most frequent adverse reactions that led to discontinuation were ILD/pneumonitis (3.7%) and pneumonia (2.2%).

In ALTA 1L, 38% of patients required a dose reduction due to adverse reactions. The most common adverse reaction that led to dose reduction was increased creatine phosphokinase (15%), increased lipase (6.6%), increased amylase (4.4%), increased aspartate aminotransferase (2.2%), ILD/pneumonitis (2.2%) and hypertension (2.2%).

Table 3 and Table 4 summarize the common adverse reactions and laboratory abnormalities observed in ALTA 1L.

Table 3: Adverse Reactions in ≥10% (All Grades [Per National Cancer Institute Common Terminology Criteria for Adverse Events (CTCAE) version 4.03]) or ≥2% (Grades 3-4) of Patients by Arm in ALTA 1L (N = 273)
Adverse Reactions | ALUNBRIG N = 136 |  | Crizotinib N = 137
Adverse Reactions | All Grades (%) | Grades 3-4 (%) | All Grades (%) | Grades 3-4 (%)
Gastrointestinal Disorders
Diarrhea | 53 | 2.2 | 57 | 2.9
Nausea | 30 | 2.2 | 58 | 2.9
Abdominal pain [Includes abdominal discomfort, abdominal distension, abdominal pain, abdominal pain lower, abdominal pain upper, and epigastric discomfort] | 24 | 0.7 | 33 | 3.6
Vomiting | 21 | 0.7 | 44 | 2.2
Constipation | 18 | 0 | 42 | 0
Stomatitis [Includes aphthous ulcer, mouth ulceration, oral mucosal blistering and stomatitis] | 13 | 0.7 | 8.8 | 0
Dyspepsia | 8 | 0 | 16 | 0.7
Gastroesophageal reflux disease | 0.7 | 0 | 11 | 0
Skin and Subcutaneous Tissue Disorders
Rash [Includes dermatitis, dermatitis acneiform, dermatitis bullous, dermatitis contact, drug eruption, erythema, palmar-plantar erythrodysesthesia syndrome, rash, rash erythematous, rash macular, rash maculo-papular, rash papular, rash pruritic, rash pustular, toxic skin eruption, urticaria] | 40 | 2.9 | 17 | 0
Pruritus [Included pruritus, allergic pruritus, and generalized pruritus] | 20 | 0.7 | 5.8 | 0.7
Respiratory, Thoracic and Mediastinal Disorders
Cough | 35 | 0 | 20 | 0
Dyspnea [Include dyspnea and exertional dyspnea] | 25 | 2.9 | 22 [Includes Grade 5 events] | 3.6
ILD/Pneumonitis | 5.1 | 2.9 | 2.2 | 0.7
Pulmonary embolism | 2.2 | 2.2 | 5.8 | 2.9
Vascular Disorders
Hypertension [Includes hypertension and systolic hypertension] | 32 | 13 | 8 | 2.9
General Disorders and Administration Site Conditions
Fatigue [Includes asthenia and fatigue] | 32 | 1.5 | 40 | 2.2
Edema [Includes angioedema, eye swelling, eyelid edema, face edema, generalized edema, lip swelling, peripheral edema, periorbital edema, peripheral swelling, skin swelling, swelling and swelling face] | 18 | 0.7 | 48 | 0.7
Pyrexia | 15 | 0.7 | 15 | 0
Musculoskeletal and Connective Tissue Disorders
Myalgia [Includes muscle spasms, muscle twitching, musculoskeletal discomfort, musculoskeletal pain, and myalgia] | 28 | 0 | 23 | 0
Back pain | 21 | 0.7 | 17 | 1.5
Arthralgia | 14 | 0 | 12 | 0
Pain in extremity | 5.1 | 0 | 15 | 0.7
Nervous System Disorders
Headache [Includes headache and migraine] | 22 | 2.2 | 17 | 0
Dizziness | 15 | 0.7 | 20 | 0.7
Peripheral neuropathy [Includes burning sensation, dysesthesia, hyperesthesia, hypoesthesia, neuralgia, peripheral neuropathy, paraesthesia, peripheral sensory neuropathy and polyneuropathy] | 11 | 0.7 | 18 | 0
Dysgeusia | 2.9 | 0 | 14 | 0
Investigations
Increased Blood cholesterol [Includes blood cholesterol increased, hypercholesterolaemia] | 13 | 0 | 0.7 | 0
Cardiac Disorders
Bradycardia [Includes bradycardia, heart rate decreased, sinus bradycardia] | 12 | 0.7 | 23 | 0
Infections and Infestations
Pneumonia [Includes lower respiratory tract infection, lung infection, pneumonia, aspiration pneumonia, and cryptococcal pneumonia] | 15 | 5.1 | 6.6 | 2.9
Upper respiratory tract infection [Includes upper respiratory tract infection and viral upper respiratory tract infection] | 12 | 0 | 10 | 0
Nasopharyngitis | 8 | 0 | 11 | 0
Urinary tract infection | 5.9 | 0.7 | 8.8 | 2.2
Metabolism and Nutrition Disorders
Decreased Appetite | 8.8 | 0.7 | 19 | 2.9
Eye Disorders
Visual Disturbance [Includes cataract, glaucoma, hypermetropia, night blindness, papilloedema, photophobia, photopsia, blurred vision, reduced visual acuity, visual field defect, visual impairment, and vitreous floaters] | 7.4 | 0 | 53 | 0.7

Table 4: Laboratory Abnormalities in ≥20% (All Grades [Per CTCAE version 4.03]) of Patients by Arm in ALTA 1L (N = 273)
Laboratory Abnormality | ALUNBRIG N = 136 [Denominator for each laboratory parameter may vary and is defined as the number of patients who had both, baseline and post-baseline test] |  | Crizotinib N = 137
Laboratory Abnormality | All Grades (%) | Grades 3-4 (%) | All Grades (%) | Grades 3-4 (%)
Chemistry
Increased creatine phosphokinase | 81 | 24 | 68 | 4.8
Increased aspartate aminotransferase | 72 | 4.5 | 70 | 5.2
Increased lipase | 59 | 17 | 36 | 9.8
Hyperglycemia [Elevated blood insulin was also observed in both arms] | 56 | 7.5 | 37 | 3.7
Increased alanine aminotransferase | 52 | 5.2 | 77 | 13
Increased amylase | 52 | 6.8 | 25 | 3
Decreased phosphorous | 41 | 3.7 | 39 | 6
Increased alkaline phosphatase | 36 | 3 | 49 | 1.5
Increased creatinine | 25 | 0 | 33 | 0
Potassium increased | 24 | 1.5 | 31 | 3.7
Increased calcium | 22 | 0 | 1.5 | 0
Decreased magnesium | 21 | 0 | 6.9 | 0
Decreased albumin | 15 | 0.8 | 52 | 3.7
Decreased calcium | 15 | 0 | 67 | 1.5
Hematology
Hemoglobin decreased | 41 | 2.3 | 36 | 1.5
Lymphocyte count decreased | 42 | 9.3 | 30 | 5.4
Neutrophil count decreased | 12 | 0 | 34 | 6.8

Clinically relevant adverse reactions in patients who received ALUNBRIG included photosensitivity (3.7%).

ALK-positive Advanced or Metastatic NSCLC Previously Treated with Crizotinib

The safety of ALUNBRIG was evaluated in 219 patients with locally advanced or metastatic ALK-positive NSCLC who received at least 1 dose of ALUNBRIG in ALTA after experiencing disease progression on crizotinib. Patients received ALUNBRIG 90 mg once daily continuously (90 mg group) or 90 mg once daily for 7 days followed by 180 mg once daily (90→180 mg group). The median duration of treatment was 7.5 months in the 90 mg group and 7.8 months in the 90→180 mg group. A total of 150 (68%) patients were exposed to ALUNBRIG for greater than or equal to 6 months and 42 (19%) patients were exposed for greater than or equal to 1 year.

The study population (N = 222) characteristics were: median age 54 years (range: 18 to 82), age less than 65 years (77%), female (57%), White (67%), Asian (31%), Stage IV disease (98%), NSCLC adenocarcinoma histology (97%), never or former smoker (95%), ECOG Performance Status (PS) 0 or 1 (93%), and CNS metastases at baseline (69%) [see Clinical Studies (14)].

Serious adverse reactions occurred in 38% of patients in the 90 mg group and 40% of patients in the 90→180 mg group. The most common serious adverse reactions were pneumonia (5.5% overall, 3.7% in the 90 mg group, and 7.3% in the 90→180 mg group) and ILD/pneumonitis (4.6% overall, 1.8% in the 90 mg group and 7.3% in the 90→180 mg group). Fatal adverse reactions occurred in 3.7% of patients and consisted of pneumonia (2 patients), sudden death, dyspnea, respiratory failure, pulmonary embolism, bacterial meningitis and urosepsis (1 patient each).

In ALTA, 2.8% of patients in the 90 mg group and 8.2% of patients in the 90→180 mg group permanently discontinued ALUNBRIG for adverse reactions. The most frequent adverse reactions that led to discontinuation were ILD/pneumonitis (0.9% in the 90 mg group and 1.8% in the 90→180 mg group) and pneumonia (1.8% in the 90→180 mg group only).

In ALTA, 14% of patients required a dose reduction due to adverse reactions (7.3% in the 90 mg group and 20% in the 90→180 mg group). The most common adverse reaction that led to dose reduction was increased creatine phosphokinase for both regimens (1.8% in the 90 mg group and 4.5% in the 90→180 mg group).

Table 5 and Table 6 summarize the common adverse reactions and laboratory abnormalities observed in ALTA.

Table 5: Adverse Reactions in ≥10% (All Grades [Per National Cancer Institute Common Terminology Criteria for Adverse Events (CTCAE) version 4.0]) or ≥2% (Grades 3-4) of Patients by Dose Group in ALTA (N = 219)
Adverse Reactions | 90 mg once daily N = 109 |  | 90→180 mg once daily N = 110
Adverse Reactions | All Grades (%) | Grades 3-4 (%) | All Grades (%) | Grades 3-4 (%)
Gastrointestinal Disorders
Nausea | 33 | 0.9 | 40 | 0.9
Diarrhea | 19 | 0 | 38 | 0
Vomiting | 24 | 1.8 | 23 | 0
Constipation | 19 | 0.9 | 15 | 0
Abdominal Pain [Includes abdominal distension, abdominal pain, and epigastric discomfort] | 17 | 0 | 10 | 0
General Disorders and Administration Site Conditions
Fatigue [Includes asthenia and fatigue] | 29 | 1.8 | 36 | 0
Pyrexia | 14 | 0 | 6.4 | 0.9
Respiratory, Thoracic and Mediastinal Disorders
Cough | 18 | 0 | 34 | 0
Dyspnea [Includes dyspnea and exertional dyspnea] | 27 | 2.8 | 21 | 1.8 [Includes one Grade 5 event]
ILD/Pneumonitis | 3.7 | 1.8 | 9.1 | 2.7
Hypoxia | 0.9 | 0 | 2.7 | 2.7
Nervous System Disorders
Headache [Includes headache and sinus headache] | 28 | 0 | 27 | 0.9
Peripheral Neuropathy [Includes peripheral sensory neuropathy and paresthesia] | 13 | 0.9 | 13 | 1.8
Skin and Subcutaneous Tissue Disorders
Rash [Includes acneiform dermatitis, exfoliative rash, rash, pruritic rash, and pustular rash] | 15 | 1.8 | 24 | 3.6
Vascular Disorders
Hypertension | 11 | 5.5 | 21 | 6.4
Musculoskeletal and Connective Tissue Disorders
Muscle Spasms | 12 | 0 | 17 | 0
Back pain | 10 | 1.8 | 15 | 1.8
Myalgia [Includes musculoskeletal pain and myalgia] | 9.2 | 0 | 15 | 0.9
Arthralgia | 14 | 0.9 | 14 | 0
Pain in extremity | 11 | 0 | 3.6 | 0.9
Metabolism and Nutrition Disorders
Decreased Appetite | 22 | 0.9 | 15 | 0.9
Eye Disorders
Visual Disturbance [Includes diplopia, photophobia, blurred vision, reduced visual acuity, visual impairment, vitreous floaters, visual field defect, macular edema, and vitreous detachment] | 7.3 | 0 | 10 | 0.9
Infections
Pneumonia | 4.6 | 2.8 | 10 | 5.5
Psychiatric Disorders
Insomnia | 11 | 0 | 7.3 | 0

Table 6: Laboratory Abnormalities in ≥20% (All Grades [Per CTCAE version 4.0]) of Patients by Regimen in ALTA (N = 219)
Laboratory Abnormality | 90 mg once daily N = 109 |  | 90→180 mg once daily N = 110
Laboratory Abnormality | All Grades (%) | Grades 3-4 (%) | All Grades (%) | Grades 3-4 (%)
Chemistry
Increased aspartate aminotransferase | 38 | 0.9 | 65 | 0
Hyperglycemia [Elevated blood insulin was observed in both regimens] | 38 | 3.7 | 49 | 3.6
Increased creatine phosphokinase | 27 | 2.8 | 48 | 12
Increased lipase | 21 | 4.6 | 45 | 5.5
Increased alanine aminotransferase | 34 | 0 | 40 | 2.7
Increased amylase | 27 | 3.7 | 39 | 2.7
Increased alkaline phosphatase | 15 | 0.9 | 29 | 0.9
Decreased phosphorous | 15 | 1.8 | 23 | 3.6
Prolonged activated partial thromboplastin time | 22 | 1.8 | 20 | 0.9
Hematology
Anemia | 23 | 0.9 | 40 | 0.9
Lymphopenia | 19 | 2.8 | 27 | 4.5

Clinically relevant adverse reactions in patients who received ALUNBRIG included photosensitivity (0.9%).

Other Adverse Reactions from Multiple Clinical Trials

In a pooled clinical trial population consisting of three studies with 274 patients treated with ALUNBRIG at the recommended dose, the following adverse reactions and laboratory abnormalities were reported: white blood cell count decreased (28%), hyponatremia (20%), hypokalemia (19%), decreased platelet count (10%), dry skin (4.7%), pain (3.3%), and musculoskeletal stiffness (1.1%).

7 DRUG INTERACTIONS

7.1 Effect of Other Drugs on ALUNBRIG

Strong or Moderate CYP3A Inhibitors

Coadministration of ALUNBRIG with a strong or moderate CYP3A inhibitor increased brigatinib plasma concentrations, which may increase the incidence of adverse reactions [see Clinical Pharmacology (12.3)]. Avoid coadministration of ALUNBRIG with strong or moderate CYP3A inhibitors. If coadministration of strong or moderate CYP3A inhibitors cannot be avoided, modify dose as recommended [see Dosage and Administration (2.4)].

Strong or Moderate CYP3A Inducers

Coadministration of ALUNBRIG with a strong or moderate CYP3A inducer decreased brigatinib plasma concentrations, which may decrease the efficacy of ALUNBRIG [see Clinical Pharmacology (12.3)]. Avoid coadministration of ALUNBRIG with strong or moderate CYP3A inducers. If coadministration of moderate CYP3A inducers cannot be avoided, modify dose as recommended [see Dosage and Administration (2.5)].

8 USE IN SPECIFIC POPULATIONS

8.1 Pregnancy

Risk Summary

Based on its mechanism of action and findings in animals, ALUNBRIG can cause fetal harm when administered to a pregnant woman [see Clinical Pharmacology (12.1)]. There are no clinical data on the use of ALUNBRIG in pregnant women. Administration of brigatinib to pregnant rats during the period of organogenesis resulted in dose-related skeletal anomalies at doses as low as 12.5 mg/kg/day (approximately 0.7 times the human exposure by AUC at 180 mg once daily) as well as increased post-implantation loss, malformations, and decreased fetal body weight at doses of 25 mg/kg/day (approximately 1.26 times the human exposure at 180 mg once daily) or greater (see Data). Advise pregnant women of the potential risk to a fetus.

In the U.S. general population, the estimated background risk of major birth defects and miscarriage in clinically recognized pregnancies is 2% to 4% and 15% to 20%, respectively.

Data

Animal Data

In an embryo-fetal development study in which pregnant rats were administered daily doses of brigatinib during organogenesis, dose-related skeletal (incomplete ossification, small incisors) and visceral anomalies were observed at doses as low as 12.5 mg/kg/day (approximately 0.7 times the human exposure by AUC at 180 mg once daily). Malformations observed at 25 mg/kg/day (approximately 1.26 times the human AUC at 180 mg once daily) included anasarca (generalized subcutaneous edema), anophthalmia (absent eyes), forelimb hyperflexion, small, short and/or bent limbs, multiple fused ribs, bent scapulae, omphalocele (intestine protruding into umbilicus), and gastroschisis (intestines protruding through a defect in the abdominal wall) along with visceral findings of moderate bilateral dilatation of the lateral ventricles.

8.2 Lactation

Risk Summary

There are no data regarding the secretion of brigatinib in human milk or its effects on the breastfed infant or milk production. Because of the potential for adverse reactions in breastfed infants, advise lactating women not to breastfeed during treatment with ALUNBRIG and for 1 week following the final dose.

8.3 Females and Males of Reproductive Potential

Pregnancy Testing

Verify pregnancy status in females of reproductive potential prior to initiating ALUNBRIG [see Use in Specific Populations (8.1)].

Contraception

ALUNBRIG can cause fetal harm [see Use in Specific Populations (8.1)].

Females

Advise females of reproductive potential to use effective contraception during treatment with ALUNBRIG and for at least 4 months after the final dose.

Males

Because of the potential for genotoxicity, advise males with female partners of reproductive potential to use effective contraception during treatment with ALUNBRIG and for at least 3 months after the final dose [see Nonclinical Toxicology (13.1)].

Infertility

Based on findings in male reproductive organs in animals, ALUNBRIG may cause reduced fertility in males [see Nonclinical Toxicology (13.1)].

8.4 Pediatric Use

The safety and effectiveness of ALUNBRIG in pediatric patients have not been established.

8.5 Geriatric Use

Of the 359 patients enrolled in the ALTA 1L ALUNBRIG arm and in ALTA, 26.7% were 65 and older and 7.5% were 75 and older. No overall differences in safety or effectiveness were observed between patients ≥65 years and younger patients.

8.6 Hepatic Impairment

No dose adjustment is recommended for patients with mild hepatic impairment (Child-Pugh A) or moderate hepatic impairment (Child-Pugh B). Reduce the dose of ALUNBRIG for patients with severe hepatic impairment (Child-Pugh C) [see Dosage and Administration (2.6), Clinical Pharmacology (12.3)].

8.7 Renal Impairment

No dose adjustment is recommended for patients with mild or moderate renal impairment [creatinine clearance (CLcr) 30 to 89 mL/min by Cockcroft-Gault]. Reduce the dose of ALUNBRIG for patients with severe renal impairment (CLcr 15 to 29 mL/min) [see Dosage and Administration (2.7), Clinical Pharmacology (12.3)].

11 DESCRIPTION

Brigatinib is a kinase inhibitor. The chemical name for brigatinib is 5-chloro-N^4-[2-(dimethylphosphoryl)phenyl]-N^2-{2-methoxy-4-[4-(4-methylpiperazin-1-yl)piperidin-1-yl]phenyl}pyrimidine-2,4-diamine. The molecular formula is C29H39ClN7O2P which corresponds to a formula weight of 584.10 g/mol. Brigatinib has no chiral centers. The chemical structure is shown below:

Brigatinib is an off-white to beige/tan solid. The pKas were determined to be: 1.73 ± 0.02 (base), 3.65 ± 0.01 (base), 4.72 ± 0.01 (base), and 8.04 ± 0.01 (base).

ALUNBRIG is supplied for oral use as film-coated tablets containing 180 mg, 90 mg or 30 mg of brigatinib and the following inactive ingredients: lactose monohydrate, microcrystalline cellulose, sodium starch glycolate (Type A), magnesium stearate, and hydrophobic colloidal silica. The tablet coating consists of talc, polyethylene glycol, polyvinyl alcohol, and titanium dioxide.

12 CLINICAL PHARMACOLOGY

12.1 Mechanism of Action

Brigatinib is a tyrosine kinase inhibitor (TKI) with in vitro activity at clinically achievable concentrations against multiple kinases including ALK, ROS1, insulin-like growth factor-1 receptor (IGF-1R), and FLT-3 as well as EGFR deletion and point mutations. Brigatinib inhibited autophosphorylation of ALK and ALK-mediated phosphorylation of the downstream signaling proteins STAT3, AKT, ERK1/2, and S6 in in vitro and in vivo assays. Brigatinib also inhibited the in vitro proliferation of cell lines expressing EML4-ALK and NPM-ALK fusion proteins and demonstrated dose-dependent inhibition of EML4-ALK-positive NSCLC xenograft growth in mice.

At clinically achievable concentrations (≤500 nM), brigatinib inhibited the in vitro viability of cells expressing EML4-ALK and 17 mutant forms associated with resistance to ALK inhibitors including crizotinib, as well as EGFR-Del (E746-A750), ROS1-L2026M, FLT3-F691L, and FLT3-D835Y. Brigatinib exhibited in vivo antitumor activity against 4 mutant forms of EML4-ALK, including G1202R and L1196M mutants identified in NSCLC tumors in patients who have progressed on crizotinib. Brigatinib also reduced tumor burden and prolonged survival in mice implanted intracranially with an ALK-driven tumor cell line.

12.2 Pharmacodynamics

Brigatinib exposure-response relationships and the time course of the pharmacodynamic response are unknown.

Cardiac Electrophysiology

The QT interval prolongation potential of ALUNBRIG was assessed in 123 patients following once daily ALUNBRIG doses of 30 mg (0.16 times the recommended dose of 180 mg) to 240 mg (1.3 times the recommended dose of 180 mg). ALUNBRIG did not prolong the QT interval to a clinically relevant extent.

12.3 Pharmacokinetics

The geometric mean (CV%) steady-state maximum concentration (Cmax) of brigatinib at ALUNBRIG doses of 90 mg and 180 mg once daily was 552 (49%) ng/mL and 1452 (60%) ng/mL, respectively, and the corresponding area under the concentration-time curve (AUC0-Tau) was 8165 (45%) ng∙h/mL and 20276 (62%) ng∙h/mL. After a single dose and multiple dosing of ALUNBRIG, systemic exposure of brigatinib was dose proportional over the dose range of 60 mg (0.3 times the recommended dose of 180 mg) to 240 mg (1.3 times the recommended dose of 180 mg) once daily. The mean accumulation ratio after repeat dosing was 1.9 to 2.4.

Absorption

Following administration of single oral doses of ALUNBRIG of 30 mg to 240 mg, the median time to peak concentration (Tmax) ranged from 1 to 4 hours.

Effect of Food

Brigatinib Cmax was reduced by 13% with no effect on AUC in healthy subjects administered ALUNBRIG after a high fat meal (approximately 920 calories, 58 grams carbohydrate, 59 grams fat and 40 grams protein) compared to the Cmax and AUC after overnight fasting.

Distribution

Brigatinib is 91% bound to human plasma proteins and the binding is not concentration-dependent. The blood-to-plasma concentration ratio is 0.69. Following oral administration of ALUNBRIG 180 mg once daily, the mean apparent volume of distribution (Vz/F) of brigatinib at steady-state was 307 L.

Elimination

Following oral administration of ALUNBRIG 180 mg once daily, the mean apparent oral clearance (CL/F) of brigatinib at steady-state is 8.9 L/h and the mean plasma elimination half-life is 25 hours.

Metabolism

Brigatinib is primarily metabolized by CYP2C8 and CYP3A4 in vitro. Following oral administration of a single 180 mg dose of radiolabeled brigatinib to healthy subjects, N-demethylation and cysteine conjugation were the two major metabolic pathways. Unchanged brigatinib (92%) was the major circulating radioactive component.

Excretion

Following oral administration of a single 180 mg dose of radiolabeled brigatinib to healthy subjects, 65% of the administered dose was recovered in feces and 25% of the administered dose was recovered in urine. Unchanged brigatinib represented 41% and 86% of the total radioactivity in feces and urine, respectively.

Specific Populations

Age, race, sex, body weight, and albumin concentration have no clinically meaningful effect on the pharmacokinetics of brigatinib.

Patients with Hepatic Impairment

Following a single dose of ALUNBRIG 90 mg, unbound brigatinib systemic exposure (AUC0-INF) was 37% higher in subjects with severe hepatic impairment (Child-Pugh C) compared to subjects with normal hepatic function. Unbound brigatinib systemic exposure (AUC0-INF) was similar between subjects with mild (Child-Pugh A) to moderate (Child-Pugh B) hepatic impairment and subjects with normal hepatic function [see Dosage and Administration (2.6)].

Patients with Renal Impairment

Following a single dose of ALUNBRIG 90 mg, unbound brigatinib systemic exposure (AUC0-INF) was 86% higher in subjects with severe renal impairment [creatinine clearance (CLcr) 15 to 29 mL/min] compared to subjects with normal renal function.

Based on a population pharmacokinetic analysis, brigatinib exposures were similar among 125 subjects with mild renal impairment (CLcr 60 to 89 mL/min), 34 subjects with moderate renal impairment (CLcr 30 to 59 mL/min) and 270 subjects with normal renal function (CLcr ≥90 mL/min) [see Dosage and Administration (2.7)].

Drug Interaction Studies

Clinical Studies

Effect of Strong and Moderate CYP3A Inhibitors on Brigatinib:

Coadministration of 200 mg twice daily doses of itraconazole (a strong CYP3A inhibitor) with a single 90 mg dose of ALUNBRIG increased brigatinib Cmax by 21% and AUC0-INF by 101%, relative to a 90 mg dose of ALUNBRIG administered alone [see Dosage and Administration (2.4), Drug Interactions (7.1)]. A moderate CYP3A inhibitor is predicted to increase the AUC of brigatinib by approximately 40%.

Effect of Strong CYP2C8 Inhibitors on Brigatinib:

Coadministration of 600 mg twice daily doses of gemfibrozil (a strong CYP2C8 inhibitor) with a single 90 mg dose of ALUNBRIG decreased brigatinib Cmax by 41% and AUC0-INF by 12%, relative to a 90 mg dose of ALUNBRIG administered alone. The effect of gemfibrozil on the pharmacokinetics of brigatinib is not clinically meaningful and the underlying mechanism for the decreased exposure of brigatinib is unknown.

Effect of Strong and Moderate CYP3A Inducers on Brigatinib:

Coadministration of 600 mg daily doses of rifampin (a strong CYP3A inducer) with a single 180 mg dose of ALUNBRIG decreased brigatinib Cmax by 60% and AUC0-INF by 80%, relative to a 180 mg dose of ALUNBRIG administered alone [see Dosage and Administration (2.5), Drug Interactions (7.1)]. A moderate CYP3A inducer is predicted to decrease the AUC of brigatinib by approximately 50%.

Effect of Brigatinib on CYP3A Substrates:

Coadministration of 180 mg daily doses of ALUNBRIG with a single 3 mg oral dose of midazolam (a sensitive CYP3A substrate) decreased midazolam Cmax by 16% and AUC0-INF by 26%, relative to a 3 mg oral dose of midazolam administered alone. Brigatinib is considered a weak inducer of CYP3A.

In Vitro Studies

Effect of Brigatinib on CYP Enzymes:

Brigatinib, at clinically relevant plasma concentrations, induced CYP3A via activation of the pregnane X receptor (PXR). Brigatinib may also induce CYP2C enzymes via the same mechanism at clinically relevant concentrations.

Brigatinib did not inhibit CYP1A2, 2B6, 2C8, 2C9, 2C19, 2D6, or 3A4/5 at clinically relevant concentrations.

Effect of P-glycoprotein and BCRP Inhibitors on Brigatinib:

Brigatinib is a substrate of the efflux transporters P-glycoprotein (P-gp) and breast cancer resistance protein (BCRP). Given that brigatinib exhibits high solubility and high permeability in vitro, P-gp and BCRP inhibitors are unlikely to increase plasma concentrations of brigatinib.

Effect of Other Transporters on Brigatinib:

Brigatinib is not a substrate of organic anion transporting polypeptide (OATP1B1, OATP1B3), organic anion transporter (OAT1, OAT3), organic cation transporter (OCT1, OCT2), multidrug and toxin extrusion protein (MATE1, MATE2K), or bile salt export pump (BSEP).

Effect of Brigatinib on Transporters:

Brigatinib is an inhibitor of P-gp, BCRP, OCT1, MATE1, and MATE2K in vitro. Therefore, brigatinib may have the potential to increase concentrations of coadministered substrates of these transporters. Brigatinib at clinically relevant concentrations did not inhibit OATP1B1, OATP1B3, OAT1, OAT3, OCT2 or BSEP.

13 NONCLINICAL TOXICOLOGY

13.1 Carcinogenesis, Mutagenesis, Impairment of Fertility

Carcinogenicity studies have not been performed with brigatinib.

Treatment with brigatinib resulted in chromosomal damage in an in vivo mammalian erythrocyte micronucleus in the rat, but was not mutagenic in the Ames or in vitro mammalian chromosome aberration tests.

Dedicated animal fertility studies were not conducted with brigatinib. Testicular toxicity was observed in repeat-dose animal studies at doses resulting in exposure as low as 0.2 times the exposure in patients at the 180 mg dose. In rats, findings included lower weight of testes, seminal vesicles and prostate gland, and testicular tubular degeneration; these effects were not reversible during the 2 month recovery period. In monkeys, findings included reduced size of testes along with microscopic evidence of hypospermatogenesis; these effects were reversible during the recovery period.

14 CLINICAL STUDIES

TKI-naïve Advanced ALK-positive NSCLC (ALTA 1L Study)

The efficacy of ALUNBRIG was demonstrated in a randomized (1:1), open-label, multicenter trial (ALTA 1L, NCT02737501) in adult patients with advanced ALK-positive NSCLC who had not previously received an ALK-targeted therapy. The study required patients to have an ALK rearrangement based on a local standard of care testing. Eligible patients were allowed to have up to 1 prior regimen of chemotherapy in the locally advanced or metastatic setting and were required to have an ECOG Performance Status of 0-2. Neurologically stable patients with treated or untreated central nervous system (CNS) metastases, including leptomeningeal metastases, were eligible. Patients with a history of interstitial lung disease, drug-related pneumonitis, or radiation pneumonitis were excluded. The major efficacy outcome measure was progression-free survival (PFS) as evaluated by a Blinded Independent Review Committee (BIRC) according to Response Evaluation Criteria in Solid Tumors (RECIST v1.1). Additional efficacy outcome measures included confirmed overall response rate (ORR), duration of response (DOR), intracranial ORR, and intracranial DOR as evaluated by BIRC, and overall survival (OS).

A total of 275 patients were randomized to receive ALUNBRIG 180 mg orally once daily with a 7-day lead-in at 90 mg once daily (n = 137) or crizotinib 250 mg orally twice daily (n = 138). Of the 275 enrolled patients, 239 had positive results using the companion diagnostic test, the Vysis ALK Break Apart FISH Probe Kit; central results were negative for 20 patients and unavailable for 16 patients. Crossover from the crizotinib arm to the ALUNBRIG arm was permitted following disease progression.

Randomization was stratified by CNS metastases (present vs absent) and prior chemotherapy use for locally advanced or metastatic disease (yes, no).

Baseline demographic characteristics of the overall study population were: median age 59 years (range: 27 to 89, 32% 65 and over), 59% White and 39% Asian, 55% female, 39% ECOG PS 0 and 56% ECOG PS 1, and 58% never smokers. The disease characteristics of the overall study population were: 93% with Stage IV disease; 27% received chemotherapy in the locally advanced or metastatic setting; 14% had received CNS radiation; 31% had bone metastases; and 20% had liver metastases. CNS metastases were present in 35% (n = 96) of patients; 41 of those patients had measurable CNS lesions.

ALTA 1L demonstrated a statistically significant improvement in PFS by BIRC. Efficacy results from this study are described in Table 7 and Figure 1.

Table 7: Efficacy Results by BIRC Assessment in ALTA 1L
Efficacy Parameters | ALUNBRIG N = 137 | Crizotinib N = 138
Progression-Free Survival
Number of Events, n (%) | 63 (46%) | 87 (63%)
Median (months) (95% CI) | 24.0 (18.5, NE) | 11.0 (9.2, 12.9)
Hazard ratio (95% CI) | 0.49 (0.35, 0.68)
p-value [Stratified by presence of iCNS metastases at baseline and prior chemotherapy for locally advanced or metastatic disease for log-rank test and Cochran Mantel-Haenszel test, respectively] | <.0001
Tumor Responses
Confirmed Overall Response Rate, % (95% CI) | 74% (66, 81) | 62% (53, 70)
p-value | 0.0342
Complete Response, % (95% CI) | 15% (9, 22) | 9% (5, 15)
Partial Response, % (95% CI) | 59% (50, 67) | 53% (44, 61)
Duration of Response
Number of Confirmed responders | n=101 | n=85
Median (months) (95% CI) [Based on final analysis data for confirmed responders observed at interim analysis] | 33.1 (22.0, NE) | 13.8 (10.4, 20.8)
CI = Confidence Interval, NE = Not Estimable

Figure 1: Kaplan-Meier Plot of Progression-Free Survival by BIRC in ALTA 1L

At the final analysis of overall survival, conducted approximately 3 years after the last patient enrolled, there were 92 deaths (33% of all patients) including 41 deaths on the ALUNBRIG arm and 51 deaths on the crizotinib arm; median OS was not reached on either arm.

BIRC assessment of confirmed intracranial ORR and intracranial DOR according to RECIST v1.1 in the subgroup of 41 patients with measurable CNS metastases (≥10 mm in longest diameter) at baseline are summarized in Table 8. Duration of intracranial response was measured from date of first intracranial response until intracranial disease progression (new lesions, intracranial target lesion diameter growth ≥20% from nadir, or unequivocal progression of intracranial nontarget lesions) or death.

Table 8: Intracranial Overall Response in Patients with Measurable CNS Metastases in ALTA 1L
Efficacy Parameter | ALUNBRIG (N = 18) | Crizotinib (N = 23)
Confirmed Intracranial Overall Response Rate, (95% CI) | 78% (52, 94) | 26% (10, 48)
Complete Response, % (95% CI) | 28% (10, 53) | 0 (0, 15)
Partial Response, % (95% CI) | 50% (26, 74) | 26% (10, 48)
Duration of Intracranial Response
Number of Confirmed Responders | n = 14 | n = 6
Intracranial Response Duration ≥24 months | 64% | NE
CI = Confidence Interval; NE = Not Estimable

ALK-positive Advanced or Metastatic NSCLC Previously Treated with Crizotinib

The efficacy of ALUNBRIG was demonstrated in a two-arm, open-label, multicenter trial (ALTA, NCT02094573) in adult patients with locally advanced or metastatic ALK-positive non-small cell lung cancer (NSCLC) who had progressed on crizotinib. The study required patients to have a documented ALK rearrangement based on an FDA-approved test or a different test with adequate archival tissue to confirm ALK arrangement by the Vysis® ALK Break-Apart fluorescence in situ hybridization (FISH) Probe Kit test. Key eligibility criteria included an ECOG Performance Status of 0-2 and progression on crizotinib. Neurologically stable patients with central nervous system (CNS) metastases were permitted to enroll. Patients with a history of interstitial lung disease or drug-related pneumonitis or who had received crizotinib within 3 days of the first dose of brigatinib were excluded. The major efficacy outcome measure was confirmed overall response rate (ORR) according to Response Evaluation Criteria in Solid Tumors (RECIST v1.1) as evaluated by an Independent Review Committee (IRC). Additional efficacy outcome measures included Investigator-assessed ORR, duration of response (DOR), intracranial ORR, and intracranial DOR.

A total of 222 patients were randomized to receive ALUNBRIG either 90 mg once daily (90 mg arm; n = 112) or 180 mg once daily following a 7-day lead-in at 90 mg once daily (90→180 mg arm; n = 110). Randomization was stratified by CNS metastases (present vs absent) and best prior response to crizotinib (complete or partial response vs any other response/unevaluable).

Baseline demographic characteristics of the overall study population were: median age 54 years (range: 18 to 82, 23% 65 and over), 67% White and 31% Asian, 57% female, 36% ECOG PS 0 and 57% ECOG PS 1, and 95% never or former smokers. The disease characteristics of the overall study population were: Stage IV disease in 98%, adenocarcinoma histology in 97%, prior systemic chemotherapy in 74%, CNS metastases in 69% (61% had received prior CNS radiation), bone metastases in 39%, and liver metastases in 26% of patients. Sixty-four percent of patients had an objective response to prior crizotinib.

The median duration of follow-up was 8 months (range: 0.1 to 20.2). Efficacy results from ALTA are summarized in Table 9.

Table 9: ALTA Efficacy Results
Efficacy Parameter | IRC Assessment |  | Investigator Assessment
Efficacy Parameter | 90 mg once daily (N = 112) | 90→180 mg once daily (N = 110) | 90 mg once daily (N = 112) | 90→180 mg once daily (N = 110)
Overall Response Rate (95% CI) | 48% (39,58) | 53% (43,62) | 45% (35,54) | 54% (44,63)
Complete Response, n (%) | 4 (3.6%) | 5 (4.5%) | 1 (0.9%) | 4 (3.6%)
Partial Response, n (%) | 50 (45%) | 53 (48%) | 49 (44%) | 55 (50%)
Duration of Response, median in months (95% CI) | 13.8 (7.4,NE) | 13.8 (9.3,NE) | 13.8 (5.6,13.8) | 11.1 (9.2,13.8)
CI = Confidence Interval; NE = Not Estimable

IRC assessment of intracranial ORR and intracranial DOR according to RECIST v1.1 in the subgroup of 44 patients with measurable CNS metastases (≥10 mm in longest diameter) at baseline are summarized in Table 10. Duration of intracranial response was measured from date of first intracranial response until intracranial disease progression (new lesions, intracranial target lesion diameter growth ≥20% from nadir, or unequivocal progression of intracranial nontarget lesions) or death.

Table 10: Intracranial Overall Response in Patients with Measurable CNS Metastases in ALTA
Efficacy Parameter | IRC Assessment
Efficacy Parameter | 90 mg once daily (N = 26) | 90→180 mg once daily (N = 18)
Intracranial Overall Response Rate, (95 % CI) | 42% (23,63) | 67% (41,87)
Complete Response, n (%) | 2 (7.7%) | 0
Partial Response, n (%) | 9 (35%) | 12 (67%)
Duration of Intracranial Response
Number of Responders | 11 | 12
Intracranial Response Duration ≥6 months | 7 (64%) | 6 (50%)
Intracranial Response Duration ≥12 months | 4 (36%) | 3 (25%)
CI = Confidence Interval

16 HOW SUPPLIED/STORAGE AND HANDLING

180 mg tablets: oval, white to off-white film-coated tablets with "U13" debossed on one side and plain on the other side; available in:

Bottle of 23 tablets | NDC 63020-180-23
Bottle of 30 tablets | NDC 63020-180-30

90 mg tablets: oval, white to off-white film-coated tablets with "U7" debossed on one side and plain on the other side; available in:

Bottle of 7 tablets | NDC 63020-090-07
Bottle of 30 tablets | NDC 63020-090-30

30 mg tablets: round, white to off-white film-coated tablets with "U3" debossed on one side and plain on the other side; available in:

Bottle of 30 tablets | NDC 63020-113-30

90 mg / 7 count tablets (NDC 63020-090-07) and 180 mg / 23 count tablets (NDC 63020-180-23) are also available in a single carton as a one-month initiation pack:

One carton containing one bottle of 90 mg tablets (7 count) and one bottle of 180 mg tablets (23 count) | NDC 63020-198-30

STORAGE AND HANDLING

Store at controlled room temperature 20°C to 25°C (68°F to 77°F); excursions permitted between 15°C to 30°C (59°F to 86°F) (see USP).

17 PATIENT COUNSELING INFORMATION

Advise the patient to read the FDA-approved patient labeling (Patient Information).

Interstitial Lung Disease (ILD)/Pneumonitis

Inform patients of the symptoms and risks of serious pulmonary adverse reactions such as ILD/pneumonitis. Advise patients to immediately report any new or worsening respiratory symptoms [see Warnings and Precautions (5.1)].

Hypertension

Advise patients of risks of hypertension and to promptly report signs or symptoms of hypertension [see Warnings and Precautions (5.2)].

Bradycardia

Advise patients to report any symptoms of bradycardia and to inform their healthcare provider about the use of heart and blood pressure medications [see Warnings and Precautions (5.3)].

Visual Disturbance

Advise patients to inform their healthcare provider of any new or worsening vision symptoms [see Warnings and Precautions (5.4)].

Creatine Phosphokinase (CPK) Elevation

Inform patients of the signs and symptoms of creatine phosphokinase (CPK) elevation and the need for monitoring during treatment. Advise patients to inform their healthcare provider of any new or worsening symptoms [see Warnings and Precautions (5.5)].

Pancreatic Enzymes Elevation

Inform patients of the signs and symptoms of pancreatitis and the need to monitor for amylase and lipase elevations during treatment [see Warnings and Precautions (5.6)].

Hepatotoxicity

Inform patients of the signs and symptoms of hepatotoxicity, and the need to monitor for aspartate aminotransferase (AST), alanine animotransferase (ALT) and total bilirubin elevations during treatment. Advise patients to inform their healthcare provider of any new or worsening symptoms [see Warnings and Precautions (5.7)].

Hyperglycemia

Inform patients of the risks of new or worsening hyperglycemia and the need to periodically monitor glucose levels. Advise patients with diabetes mellitus or glucose intolerance that antihyperglycemic medications may need to be adjusted during treatment with ALUNBRIG [see Warnings and Precautions (5.8)].

Photosensitivity

Inform patients of the signs and symptoms of photosensitivity. Advise patients to limit sun exposure while taking ALUNBRIG and for at least 5 days after the final dose. Advise patients to wear a hat, protective clothing, and to use a broad-spectrum Ultraviolet A (UVA)/ Ultraviolet B (UVB) sunscreen and lip balm (SPF ≥30) to protect against sunburn [see Warnings and Precautions (5.9)].

Females and Males of Reproductive Potential

Embryo-Fetal Toxicity

Advise females and males of reproductive potential that ALUNBRIG can cause fetal harm [see Warnings and Precautions (5.10), Use in Specific Populations (8.1)].

- Advise females of reproductive potential to inform their healthcare provider of a known or suspected pregnancy and to use effective contraception during treatment with ALUNBRIG and for at least 4 months after the final dose [see Use in Specific Populations (8.3)].
- Advise males with female partners of reproductive potential to use effective contraception during treatment with ALUNBRIG and for at least 3 months after the final dose [see Use in Specific Populations (8.3)].

Lactation

Advise females not to breastfeed during treatment with ALUNBRIG and for at least 1 week following the final dose [see Use in Specific Populations (8.2)].

Infertility

Advise males of reproductive potential of the potential for reduced fertility from ALUNBRIG [see Use in Specific Populations (8.3), Nonclinical Toxicology (13.1)].

Drug Interactions

Advise patients to inform their healthcare provider of all concomitant medications, including prescription medicines, over-the-counter drugs, vitamins, and herbal products. Inform patients to avoid grapefruit or grapefruit juice while taking ALUNBRIG [see Drug Interactions (7)].

Dosing and Administration

Instruct patients to start with 90 mg of ALUNBRIG once daily for the first 7 days and if tolerated, increase the dose to 180 mg once daily. Advise patients to take ALUNBRIG with or without food [see Dosage and Administration (2.2)].

Missed Dose

Advise patients that if a dose of ALUNBRIG is missed or if the patient vomits after taking a dose of ALUNBRIG, not to take an extra dose, but to take the next dose at the regular time [see Dosage and Administration (2.2)].

Distributed by:
Takeda Pharmaceuticals America, Inc.
Cambridge, MA 02142

ALUNBRIG and are registered trademarks of ARIAD Pharmaceuticals, Inc.

©2024 ARIAD Pharmaceuticals, Inc. All rights reserved.

ABG346 R6

PATIENT INFORMATION
ALUNBRIG® (uh-lun-brig)
(brigatinib)
tablets

What is the most important information I should know about ALUNBRIG?
ALUNBRIG can cause serious side effects, including:

- Lung problems. ALUNBRIG may cause severe or life-threatening swelling (inflammation) of the lungs any time during treatment, and can lead to death. These lung problems happen especially within the first week of treatment with ALUNBRIG. Symptoms may be similar to those symptoms from lung cancer. Tell your healthcare provider right away if you have any new or worsening symptoms, including:

- trouble breathing or shortness of breath
- chest pain

- cough with or without mucus
- fever

- High blood pressure (hypertension). ALUNBRIG may cause high blood pressure. Your healthcare provider will check your blood pressure before starting and during treatment with ALUNBRIG. Tell your healthcare provider right away if you get headaches, dizziness, blurred vision, chest pain or shortness of breath.
- Slow heart rate (bradycardia). ALUNBRIG may cause very slow heartbeats that can be severe. Your healthcare provider will check your heart rate during treatment with ALUNBRIG. Tell your healthcare provider right away if you feel dizzy, lightheaded, or faint during treatment with ALUNBRIG. Tell your healthcare provider if you take any heart or blood pressure medicines.
- Vision problems. ALUNBRIG may cause vision problems. Your healthcare provider may stop ALUNBRIG and refer you to an eye specialist if you develop severe vision problems during treatment with ALUNBRIG. Tell your healthcare provider right away if you have any loss of vision or any change in vision, including:

- double vision
- seeing flashes of light
- blurry vision

- light hurting your eyes
- new or increased floaters

- Muscle pain, tenderness, and weakness (myalgia). ALUNBRIG may increase the level of an enzyme in your blood called creatine phosphokinase (CPK), which may be a sign of muscle damage. Your healthcare provider will do blood tests to check your blood levels of CPK during treatment with ALUNBRIG. Tell your healthcare provider right away if you get new or worsening signs and symptoms of muscle problems, including unexplained muscle pain or muscle pain that does not go away, tenderness, or weakness.
- Inflammation of the pancreas (pancreatitis). ALUNBRIG may increase enzymes in your blood called amylase and lipase, which may be a sign of pancreatitis. Your healthcare provider will do blood tests to check your pancreatic enzyme blood levels during treatment with ALUNBRIG. Tell your healthcare provider right away if you get new or worsening signs and symptoms of pancreatitis, including upper abdominal pain that may spread to the back and get worse with eating, weight loss, or nausea.
- Liver problems (hepatotoxicity). ALUNBRIG may increase the levels of bilirubin in your blood and enzymes called aspartate aminotransferase (AST) and alanine aminotransferase (ALT) in your blood, which may be a sign of liver problems. Your healthcare provider will do blood tests to check your liver during treatment with ALUNBRIG. Tell your healthcare provider right away if you get new or worsening signs or symptoms, including:

- yellowing of your skin or the white part of your eyes
- dark or brown (tea color) urine
- nausea or vomiting
- pain on the right side of your stomach area

- bleed or bruise more easily than normal
- itchy skin
- decreased appetite
- feeling tired

- High blood sugar (hyperglycemia). ALUNBRIG may increase your blood sugar levels. Your healthcare provider will do blood tests to check your blood sugar levels before starting and during treatment with ALUNBRIG. Your healthcare provider may need to start or change your blood sugar medicine to control your blood sugar levels. Tell your healthcare provider right away if you get new or worsening signs and symptoms of hyperglycemia, including:

- feeling very thirsty
- needing to urinate more than usual
- feeling very hungry

- feeling sick to your stomach
- feeling weak or tired
- feeling confused

See "What are the possible side effects of ALUNBRIG?" for information about side effects.

What is ALUNBRIG?
ALUNBRIG is a prescription medicine used to treat adults with non-small cell lung cancer (NSCLC):

- that has a certain type of abnormal anaplastic lymphoma kinase (ALK) gene, and
- that has spread to other parts of your body.

It is not known if ALUNBRIG is safe and effective in children.

Before you take ALUNBRIG, tell your healthcare provider about all of your medical conditions, including if you:

- have lung or breathing problems
- have high blood pressure
- have a slow heartbeat
- have any vision problems
- have or have had pancreatitis
- have liver problems
- have diabetes mellitus or glucose intolerance
- have kidney problems or are on dialysis
- are pregnant or plan to become pregnant. ALUNBRIG can harm your unborn baby. Your healthcare provider will determine whether or not you are pregnant before you start treatment with ALUNBRIG. Tell your healthcare provider right away if you become pregnant during treatment with ALUNBRIG or think you may be pregnant.
  - Females who are able to become pregnant should use effective birth control during treatment with ALUNBRIG and for at least 4 months after the final dose of ALUNBRIG. Talk to your healthcare provider about birth control choices that are right for you during treatment with ALUNBRIG.
  - Males who have female partners that are able to become pregnant should use effective birth control during treatment with ALUNBRIG and for at least 3 months after the final dose of ALUNBRIG.
- are breastfeeding or plan to breastfeed. It is not known if ALUNBRIG passes into your breast milk. Do not breastfeed during treatment with ALUNBRIG and for 1 week after the final dose of ALUNBRIG.

Tell your healthcare provider about all the medicines you take, including prescription medicines, over-the-counter medicines, vitamins, or herbal supplements.

How should I take ALUNBRIG?

- Take ALUNBRIG exactly as your healthcare provider tells you to take it. Do not change your dose or stop taking ALUNBRIG unless your healthcare provider tells you to.
- Your healthcare provider will start you on a low dose (90 mg) of ALUNBRIG for the first 7 days of treatment. If you tolerate this dose of ALUNBRIG well, your healthcare provider may increase your dose after the first 7 days of treatment.
- Your healthcare provider may change your dose, temporarily stop, or permanently stop treatment with ALUNBRIG if you develop side effects.
- Take ALUNBRIG 1 time each day.
- Take ALUNBRIG with or without food.
- Swallow ALUNBRIG tablets whole. Do not crush or chew tablets.
- If you miss a dose of ALUNBRIG, do not take the missed dose. Take your next dose at your regular time.
- If you vomit after taking a dose of ALUNBRIG, do not take an extra dose. Take your next dose at your regular time.

What should I avoid while taking ALUNBRIG?

- Limit your time in the sun during treatment with ALUNBRIG and for at least 5 days after your final dose. ALUNBRIG may make your skin sensitive to sunlight. You may burn more easily and get severe sunburns. When you are in the sun, wear a hat and protective clothing, and use a broad-spectrum sunscreen and lip balm with a Sun Protection Factor (SPF) of 30 or greater to protect against sunburn.
- Avoid eating grapefruit or drinking grapefruit juice during treatment with ALUNBRIG. Grapefruit may increase the amount of ALUNBRIG in your blood.

What are the possible side effects of ALUNBRIG?
ALUNBRIG may cause serious side effects, including:

- See "What is the most important information I should know about ALUNBRIG?".

The most common side effects of ALUNBRIG include:

- diarrhea
- fatigue
- nausea
- rash

- cough
- muscle pain
- headache

- high blood pressure
- vomiting
- difficulty breathing

ALUNBRIG may cause fertility problems in males. This may affect your ability to father a child. Talk to your healthcare provider if you have concerns about fertility.
These are not all of the possible side effects of ALUNBRIG.
Call your doctor for medical advice about side effects. You may report side effects to FDA at 1-800-FDA-1088.

How should I store ALUNBRIG?

- Store ALUNBRIG at room temperature between 68°F to 77°F (20°C to 25°C).

Keep ALUNBRIG and all medicines out of the reach of children.

General information about the safe and effective use of ALUNBRIG.
Medicines are sometimes prescribed for purposes other than those listed in a Patient Information leaflet. Do not use ALUNBRIG for a condition for which it was not prescribed. Do not give ALUNBRIG to other people, even if they have the same symptoms you have. It may harm them.
You can ask your healthcare provider or pharmacist for information about ALUNBRIG that is written for health professionals.

What are the ingredients in ALUNBRIG?
Active ingredient: brigatinib
Inactive ingredients: lactose monohydrate, microcrystalline cellulose, sodium starch glycolate (Type A), magnesium stearate, and hydrophobic colloidal silica. The tablet coating consists of talc, polyethylene glycol, polyvinyl alcohol, and titanium dioxide.
Distributed by: Takeda Pharmaceuticals America, Inc., Cambridge, MA 02142

ALUNBRIG and are registered trademarks of ARIAD Pharmaceuticals, Inc.

©2024 ARIAD Pharmaceuticals, Inc. All rights reserved.
For more information, go to www.alunbrig.com or call 1-844-217-6468. ABG346 R6

This Patient Information has been approved by the U.S. Food and Drug Administration.

Revised: October 2024

PRINCIPAL DISPLAY PANEL - 30 mg Tablet Bottle Carton

NDC 63020-113-30

ALUNBRIG®
(brigatinib) tablets

30 mg

Rx Only

30 Tablets

PRINCIPAL DISPLAY PANEL - 90 mg Tablet Bottle Carton

NDC 63020-090-30

ALUNBRIG®
(brigatinib) tablets

90 mg

Rx Only

30 Tablets

PRINCIPAL DISPLAY PANEL - 180 mg Tablet Bottle Carton

NDC 63020-180-30

ALUNBRIG®
(brigatinib) tablets

180 mg

Rx Only

30 Tablets

PRINCIPAL DISPLAY PANEL - Kit Carton

NDC 63020-198-30
INITIATION PACK

ALUNBRIG®
(brigatinib) tablets

Rx Only | Oral Use

Usual Dose: One 90 mg tablet orally once daily for the first 7 days;
if tolerated, increase to one 180 mg tablet orally once daily.
See accompanying full Prescribing Information for complete details.

90 mg

7 Tablets

Take 1 tablet on
Day 1 - Day 7

180 mg

23 Tablets

Take 1 tablet on
Day 8 - Day 30